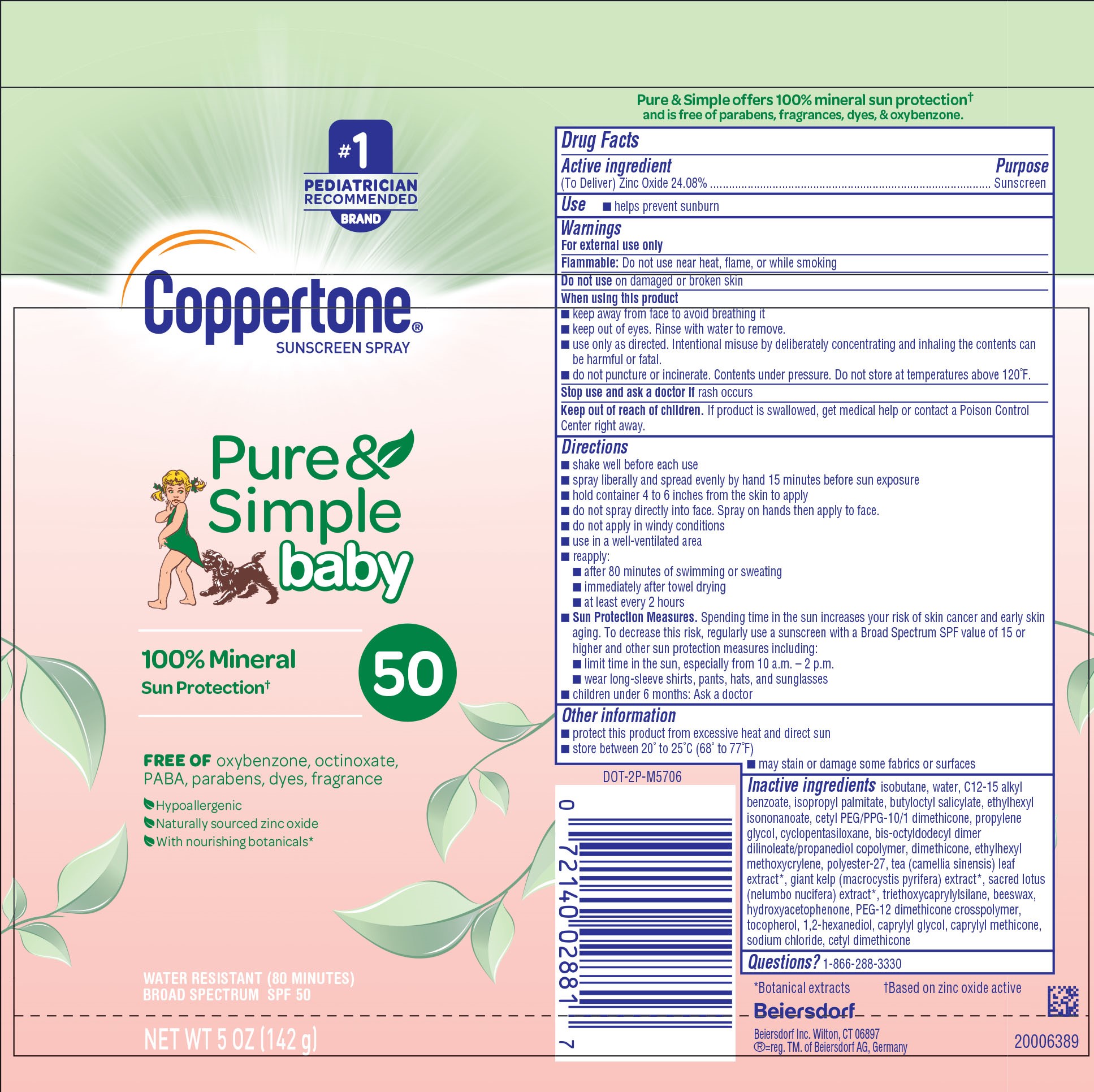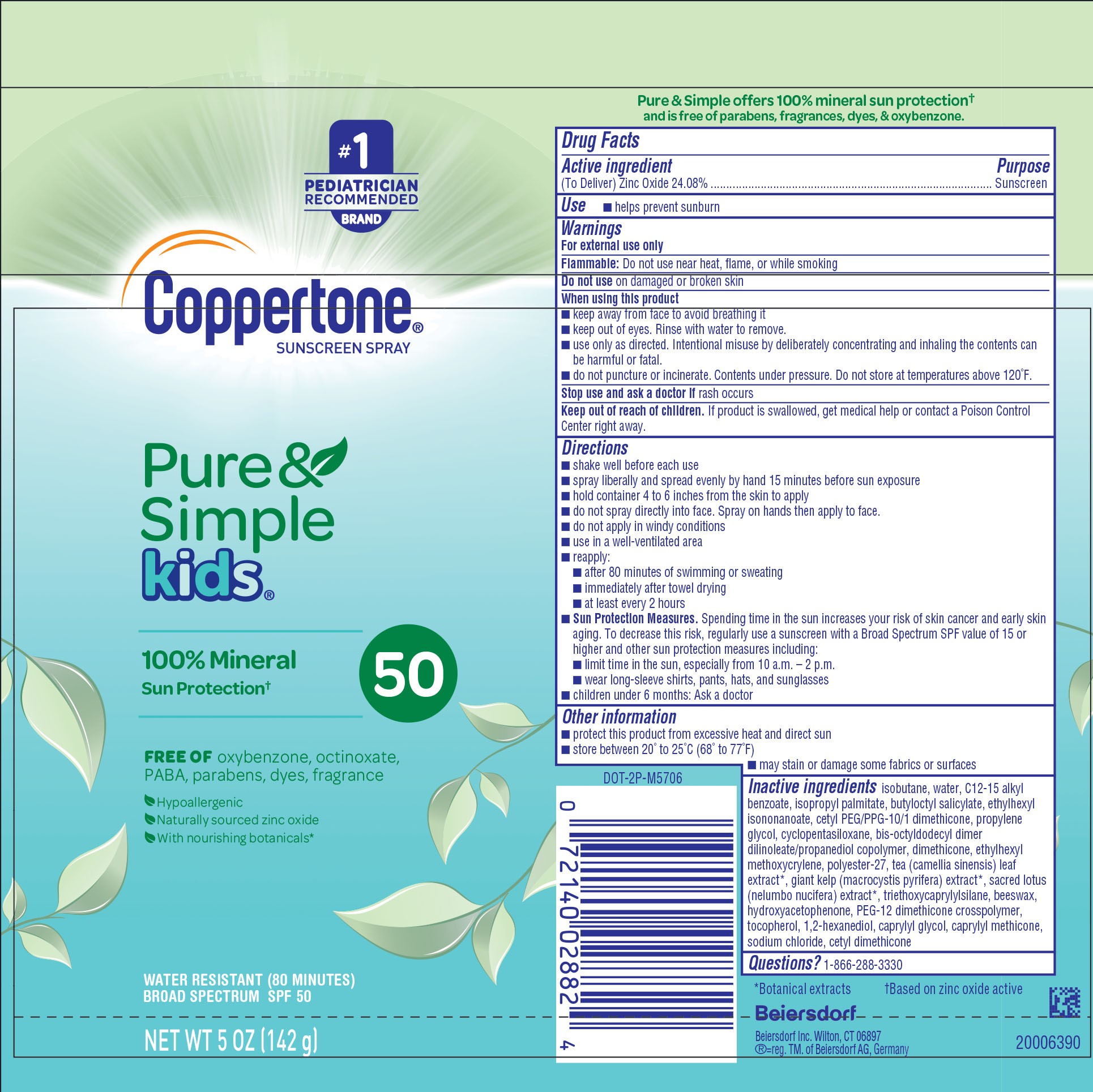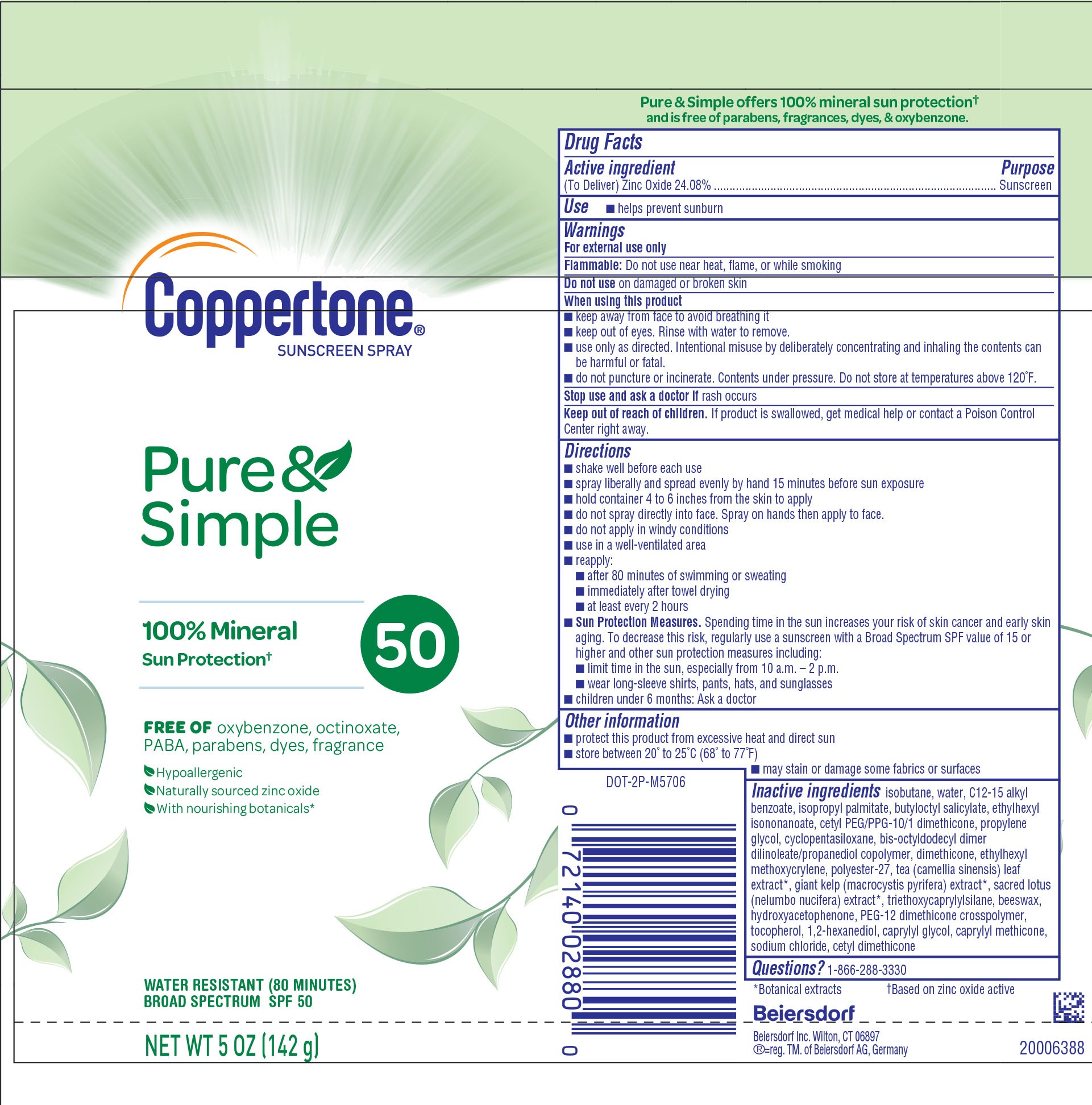 DRUG LABEL: Coppertone Pure and Simple Sunscreen SPF 50
NDC: 66800-4744 | Form: AEROSOL, SPRAY
Manufacturer: Beiersdorf Inc
Category: otc | Type: HUMAN OTC DRUG LABEL
Date: 20251231

ACTIVE INGREDIENTS: ZINC OXIDE 240.8 mg/1 g
INACTIVE INGREDIENTS: PROPYLENE GLYCOL; CYCLOMETHICONE 5; DIMETHICONE; ETHYLHEXYL METHOXYCRYLENE; POLYESTER-7; ISOBUTANE; WATER; ALKYL (C12-15) BENZOATE; BUTYLOCTYL SALICYLATE; ETHYLHEXYL ISONONANOATE; ISOPROPYL PALMITATE; CETYL PEG/PPG-10/1 DIMETHICONE (HLB 2); BIS-OCTYLDODECYL DIMER DILINOLEATE/PROPANEDIOL COPOLYMER; GREEN TEA LEAF; MACROCYSTIS PYRIFERA; SYNTHETIC BEESWAX; CAPRYLYL TRISILOXANE; SODIUM CHLORIDE; TOCOPHEROL; 1,2-HEXANEDIOL; NELUMBO NUCIFERA LEAF; TRIETHOXYCAPRYLYLSILANE; HYDROXYACETOPHENONE; PEG-12 DIMETHICONE (300 CST); CAPRYLYL GLYCOL; CETYL DIMETHICONE 150

Pure & Simple Spray SPF 50
Pure & Simple Kids Spray SPF 50
Pure & Simple Baby Sprays SPF 50

Drug Facts

Active Ingredient

(To Deliver) Zinc Oxide 24.08%

Purpose

Sunscreen

Use

helps prevent sunburn

Warnings

For external use only

Flammable:Do not use near heat, flame, or while smoking

Do not useon damaged or broken skin

DO NOT USE

■ keep away from face to avoid breathing it

■ keep out of eyes. Rinse with water to remove.

■ use only as directed. Intentional misuse by deliberately concentrating and inhaling the contents can be harmful or fatal.

■ do not puncture or incinerate. Contents under pressure. Do not store at temperatures above 120˚F.

Stop use and ask a doctor ifrash occurs

Keep out of reach of children.If product is swallowed, get medical help or contact a Poison Control Center right away.

Directions

■ shake well before each use

■ spray liberally and spread evenly by hand 15 minutes before sun exposure

■ hold container 4 to 6 inches from the skin to apply

■ do not spray directly into face. Spray on hands then apply to face.

■ do not apply in windy conditions

■ use in a well-ventilated area

■ reapply:

■ after 80 minutes of swimming or sweating

■ immediately after towel drying

■ at least every 2 hours

■ Sun Protection Measures.Spending time in the sun increases your risk of skin cancer and early skin aging. To decrease this risk, regularly use a sunscreen with a Broad Spectrum SPF value of 15 or higher and other sun protection measures including:

■ limit time in the sun, especially from 10 a.m. – 2 p.m.

■ wear long-sleeve shirts, pants, hats, and sunglasses

■ children under 6 months: Ask a doctor

Other Information

■ protect this product from excessive heat and direct sun

■ store between 20˚ to 25˚C (68˚ to 77˚F)

■ may stain or damage some fabrics or surfaces

Inactive Ingredients

isobutane, water, C12-15 alkyl benzoate, isopropyl palmitate, butyloctyl salicylate, ethylhexyl isononanoate, cetyl PEG/PPG-10/1 dimethicone, propylene glycol, cyclopentasiloxane, bis-octyldodecyl dimer dilinoleate/propanediol copolymer, dimethicone, ethylhexyl methoxycrylene, polyester-27, tea (camellia sinensis) leaf extract*, giant kelp (macrocystis pyrifera) extract*, sacred lotus (nelumbo nucifera) extract*, triethoxycaprylylsilane, beeswax, hydroxyacetophenone, PEG-12 dimethicone crosspolymer, tocopherol, 1,2-hexanediol, caprylyl glycol, caprylyl methicone, sodium chloride, cetyl dimethicone

Questions?

1-866-288-3330

PACKAGE LABEL

Coppertone®Sunscreen Spray

Pure&Simple

100% Mineral Sun Protection†

Free ofoxybenzone, octinoxate, PABA, parabens, dyes, fragrance

Hypoallergenic

Naturally sourced zinc oxide

With nourishing botanicals*

Water Resistanct (80 minutes)

Broad Specturm SPF 50

NET WT 5 OZ (142 g)